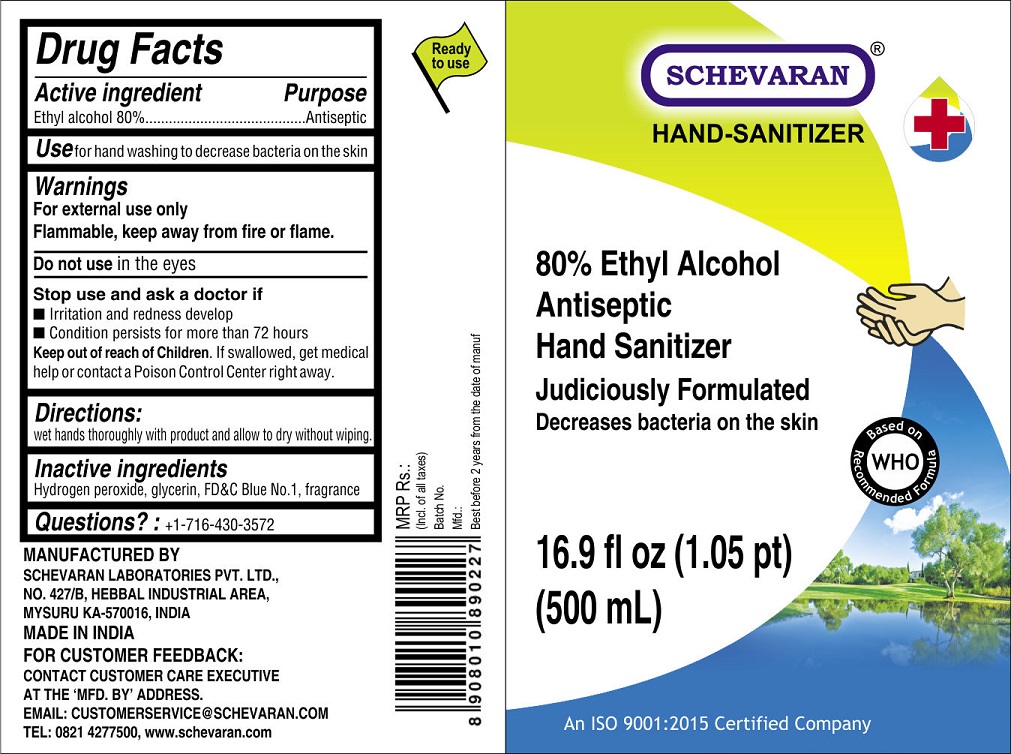 DRUG LABEL: 80 Ethyl Alcohol Antiseptic Hand Sanitizer
NDC: 82444-001 | Form: LIQUID
Manufacturer: SCHEVARAN LABORATORIES PRIVATE LIMITED
Category: otc | Type: HUMAN OTC DRUG LABEL
Date: 20220310

ACTIVE INGREDIENTS: ALCOHOL 80 mL/100 mL
INACTIVE INGREDIENTS: HYDROGEN PEROXIDE; GLYCERIN; FD&C BLUE NO. 1

80% Ethyl Alcohol Antiseptic Hand Sanitizer

Active ingredient

Ethyl alcohol 80%

Purpose

Antiseptic

Use

for hand washing to decrease bacteria on the skin

Warnings

For external use only

Flammable, keep away from fire or flame.

Do not use

in the eyes

Stop use and ask a doctor if

- Irritation and redness develop
- Condition persists for more than 72 hours

Keep out of reach of children.

If swallowed, get medical help or contact a Poison Control Center right away.

Directions:

wet hands thoroughly with product and allow to dry without wiping.

Inactive ingredients

Hydrogen peroxide, glycerin, FD&C Blue No. 1, fragrance

Questions? :

+1-716-430-3572